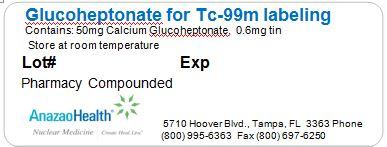 DRUG LABEL: Glucoheptonate
NDC: 51808-213 | Form: INJECTION, POWDER, LYOPHILIZED, FOR SOLUTION
Manufacturer: AnazaoHealth Corporation
Category: prescription | Type: HUMAN PRESCRIPTION DRUG LABEL
Date: 20120523

ACTIVE INGREDIENTS: CALCIUM GLUCEPTATE 50 mg/1 1
INACTIVE INGREDIENTS: STANNOUS CHLORIDE 0.6 mg/1 1

Glucoheptonate

Dear Medical Professional,

Per your order, we have compounded Glucoheptonate as a sterile freeze-dried mixture. The characteristics of this preparation are

DESCRIPTION

AnazaoHealth supplies compounded Glucoheptonate for the preparation of Tc 99m Glucoheptonate. Each vial contains 50 mg calcium glucoheptonate and 0.6 mg tin metal as stannous chloride. The vial is back filled with inert gas and may contain a partial vacuum.

CLINICAL PHARMACOLOGY

When injected intravenously, Technetium Tc 99m Glucoheptonate is rapidly cleared from the blood. In patients with normal renal function, less than 15% of the initial activity remains in the blood after one hour. About 40% of the injected dose is excreted in the urine in one hour, while about 70% is excreted in 24 hours. In patients with renal disease, the blood clearance and urinary excretion of the radiopharmaceutical are delayed.

Up to 15% of the injected dose is retained in the kidneys. The renal retention is greater in the cortex than in the medulla. The radiopharmaceutical may be bound to the proximal convoluted tubules, which are located primarily in the renal cortex.

Technetium Tc 99m Glucoheptonate tends to accumulate in intracranial lesions that are associated with excessive neovascularity or an altered blood-brain barrier. The drug does not accumulate in the choroid plexus or salivary glands.

INDICATIONS AND USAGE

Tc 99m Glucoheptonate may be used to image the kidney and brain and to assess renal and brain perfusion.

PREPARATION

Preparation of Technetium Tc 99m Glucoheptonate is done by the following aseptic procedure:

1. Waterproof gloves should be worn during the preparation procedure.
2. Snap off the plastic lid and place room temperature reaction vial in an appropriate lead shield.
3. Swab the rubber closure of the vial with a germicide.
4. Inject 1 - 5 ml sterile, additive free sodium pertechnetate Tc 99m injection containing up to 5,920 MBq (160 mCi) into the vial. Be sure to maintain inert atmosphere in vial by introducing as little air as possible during reconstitution. NOTE: If sodium pertechnetate Tc 99m injection must be diluted, use only preservative free Sodium Chloride Injection USP.
5. Secure the lead shield cover. Swirl the vial gently to mix contents and let stand 3 to 5 minutes prior to use.
6. Record the date and time of preparation on a pressure-sensitive label.
7. Affix pressure-sensitive label to shield.
8. Examine vial contents; if the solution is not clear and free of particulate matter and/or discoloration on visual inspection, it should not be used.
9. Measure the radioactivity by suitable calibration system and record prior to patient administration.
10. Appropriate quality control is recommended.
11. Injection should be administered within 12 hours of preparation.

Storage and Handling

This preparation should be stored at room temperature before and after reconstitution.

PACKAGE LABEL.PRINCIPAL DISPLAY PANEL

Figure 1